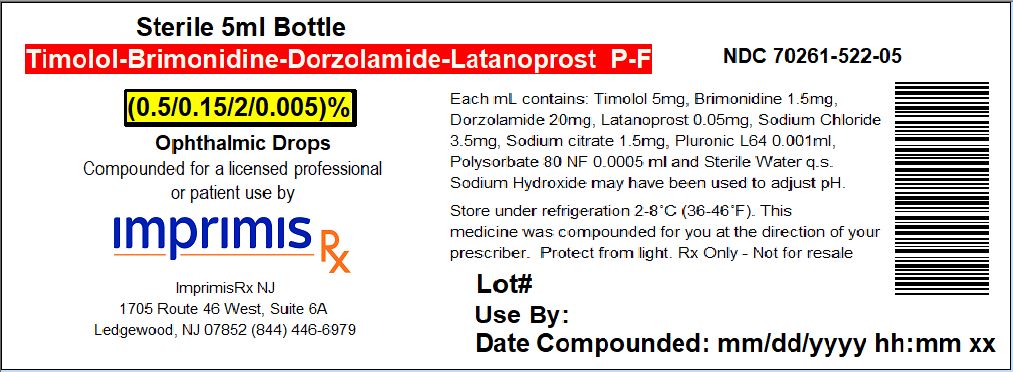 DRUG LABEL: Tim-Brim-Dor-Lat
NDC: 70261-522 | Form: SOLUTION/ DROPS
Manufacturer: ImprimisRx NJ
Category: prescription | Type: HUMAN PRESCRIPTION DRUG LABEL
Date: 20180508

ACTIVE INGREDIENTS: DORZOLAMIDE HYDROCHLORIDE 20 mg/1 mL; BRIMONIDINE TARTRATE 1.5 mg/1 mL; LATANOPROST 0.05 mg/1 mL; TIMOLOL MALEATE 5 mg/1 mL

STORAGE AND HANDLING

Store under refrigeration 2° to 8° C (36° to 46° F)

Bottle Label